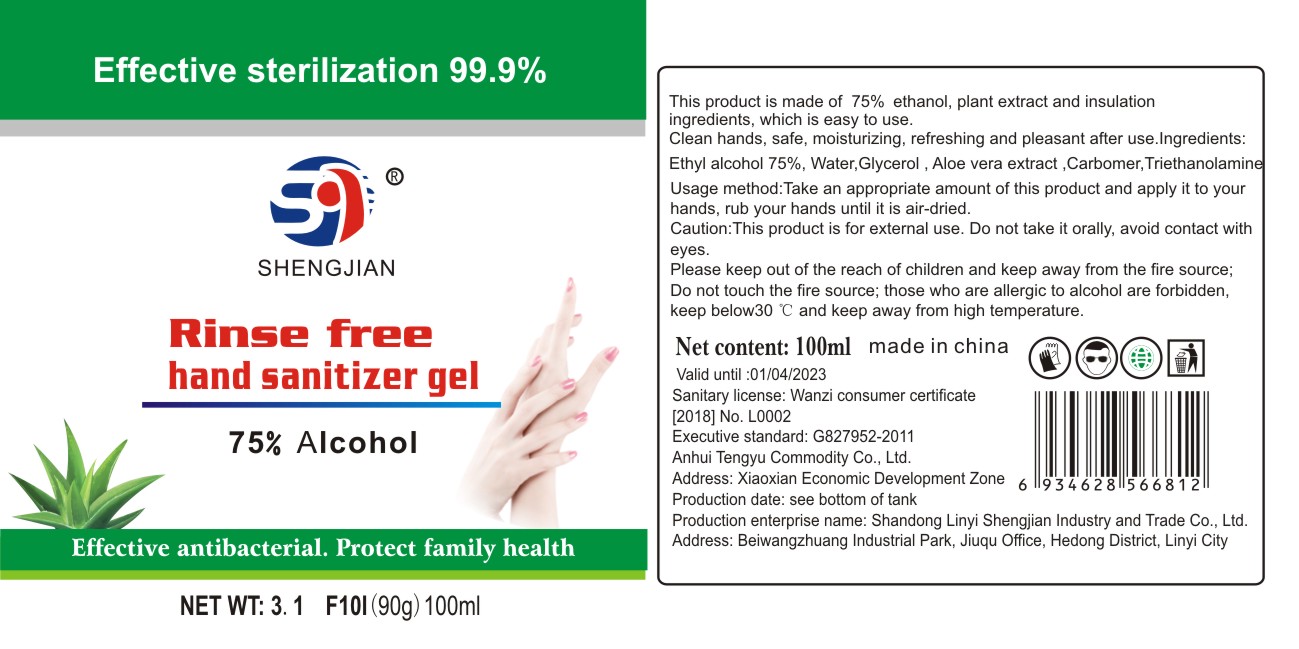 DRUG LABEL: Rinse free hand sanitizer
NDC: 78024-002 | Form: GEL
Manufacturer: LINYI SHENGJIAN INDUSTRY & TRADE CO., LTD
Category: otc | Type: HUMAN OTC DRUG LABEL
Date: 20200519

ACTIVE INGREDIENTS: ALCOHOL 75 mL/100 mL
INACTIVE INGREDIENTS: ALOE VERA LEAF; TROLAMINE; GLYCERIN; CARBOMER HOMOPOLYMER, UNSPECIFIED TYPE; WATER

Hand Sanitizer

Active Ingredient(s)

Ethyl alcohol 75%.

Purpose

Effective antibacterial.Protect family health.

Usage method

Take an appropriate amount of this product and apply it to your hands,rub your hands until it is air-dried.

Warnings

- This product is for external use.Do not take it orally,avoid contact with eyes.
- Please keep out of the reach of children and keep away from the fire souse.
- Do not touch the fire source； those who are allergic to alcohol are forbidden.
- keep below 30℃ and keep away from high temperature.

When using

Clean hands,safe，moisturizing，refreshing and pleasant after use.

Inactive ingredients

Water,Glycerol,Aloe vera extract,Carbomer,Triethanolamine.